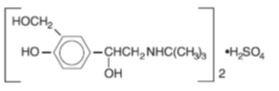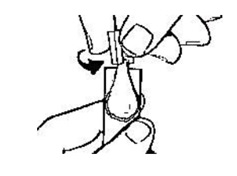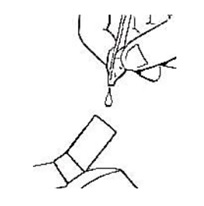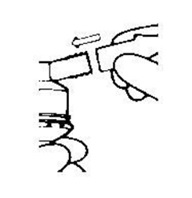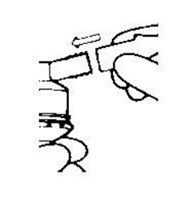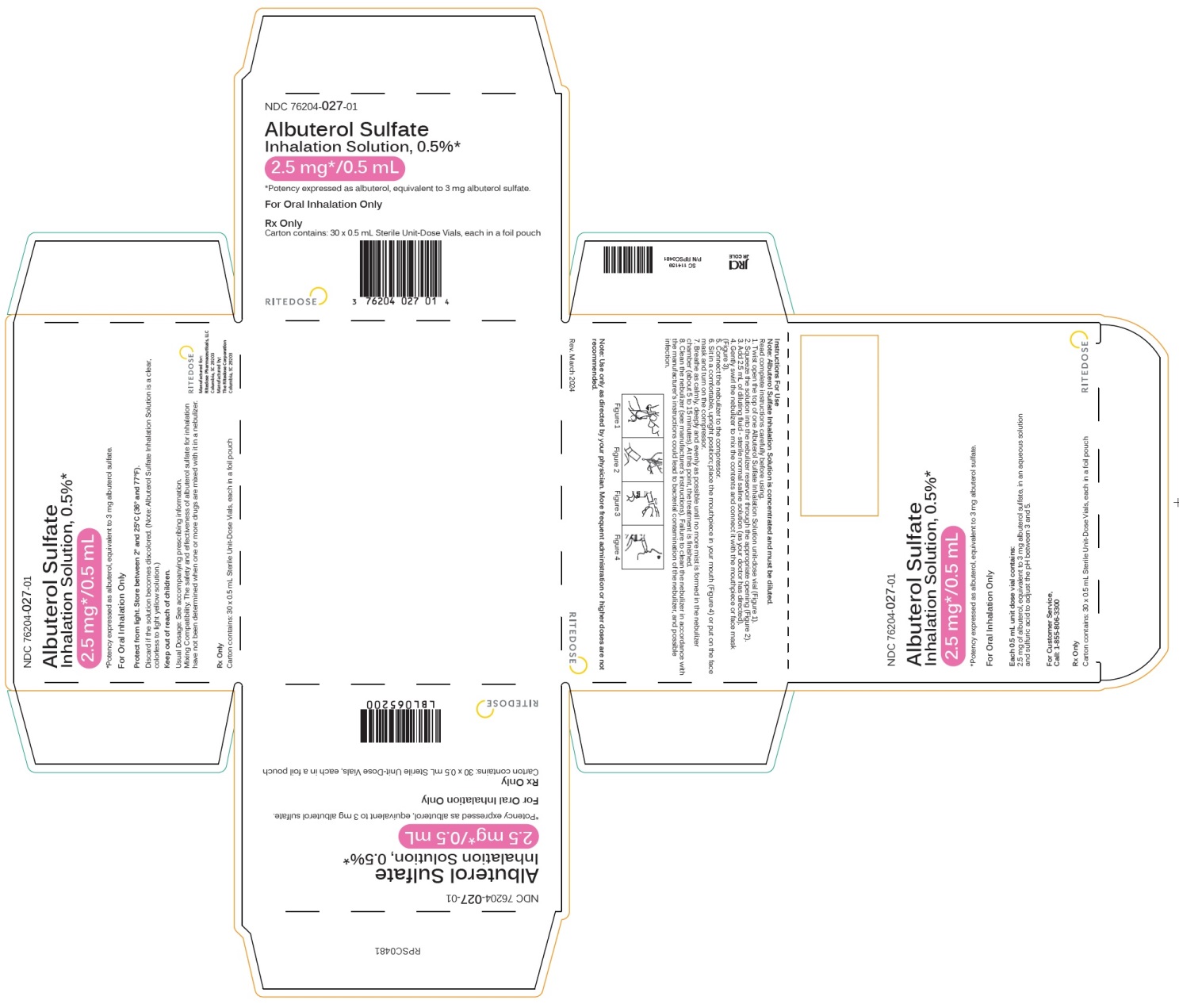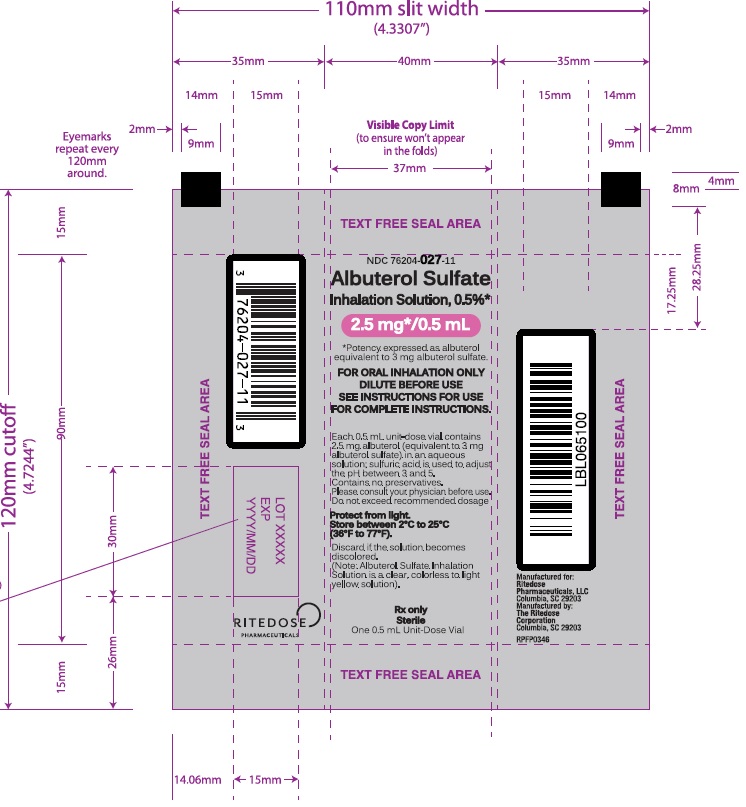 DRUG LABEL: Albuterol Sulfate Inhalation Solution, 0.5%
NDC: 76204-027 | Form: SOLUTION
Manufacturer: Ritedose Pharmaceuticals, LLC
Category: prescription | Type: HUMAN PRESCRIPTION DRUG LABEL
Date: 20251210

ACTIVE INGREDIENTS: ALBUTEROL SULFATE 2.5 mg/0.5 mL
INACTIVE INGREDIENTS: SULFURIC ACID; WATER

Albuterol Sulfate Inhalation Solution, EQ 0.5% Base (2.5 mg/0.5 mL)

Albuterol Sulfate Inhalation Solution

0.5%2.5 mg* / 0.5 mL

(*Equivalent to 3 mg of albuterol sulfate)

*Potency expressed as albuterol

DESCRIPTION

Albuterol Sulfate Inhalation Solution, 0.5% contains albuterol sulfate, USP, the racemic form of albuterol and a relatively selective beta2- adrenergic bronchodilator. Albuterol sulfate has the chemical name α1[(tert-Butylamino) methyl]-4-hydroxy-m-xylene-α, α’-diol sulfate (2:1) (salt), and the following chemical structure:

The molecular weight of albuterol sulfate is 576.7, and the empirical formula is (C13H21NO3)2• H2SO4. Albuterol sulfate is a white crystalline powder, soluble in water and slightly soluble in ethanol. The World Health Organization’s recommended name for albuterol base is salbutamol.

Albuterol sulfate inhalation solution, 0.5%, is in concentrated form. Dilute 0.5 mL of the solution to 3 mL with sterile normal saline solution prior to administration by nebulization.

Each 0.5 mL Unit-Dose Vial Contains:2.5 mg of albuterol (equivalent to 3 mg of albuterol sulfate, USP) in a sterile, aqueous solution; sulfuric acid is used to adjust the pH to between 3 and 5. Albuterol Sulfate Inhalation solution contains no sulfiting agents or preservatives. It is supplied in 0.5 mL sterile Unit-Dose Vials.

Albuterol sulfate inhalation solution is a clear, colorless to light yellow solution.

CLINICAL PHARMACOLOGY

The primary action of beta-adrenergic drugs, is to stimulate adenyl cyclase, the enzyme that catalyzes the formation of cyclic-3' ,5'-adenosine monophosphate (cyclic AMP) from adenosine triphosphate (ATP) in beta-adrenergic cells. The cyclic AMP thus fanned mediates the cellular responses. Increased cyclic AMP levels are associated with relaxation of bronchial smooth muscle and inhibition of release of mediators of immediate hypersensitivity from cells, especially from mast cells.

In vitrostudies and in vivopharmacologic studies have demonstrated that albuterol has a preferential effect on beta2-adrenergic receptors compared with isoproterenol. While it is recognized that beta2-adrenergic receptors are the predominant receptors in bronchial smooth muscle, data indicate that there is a population of beta2-receptors in the human heart existing in a concentration between 10% and 50%. The precise function of these receptors has not been established.

In controlled clinical trials, albuterol has been shown in most controlled clinical trials to have more effect on the respiratory tract, in the form of bronchial smooth muscle relaxation, than isoproterenol at comparable doses while producing fewer cardiovascular effects.

Controlled clinical studies and other clinical experience have shown that inhaled albuterol, like other beta-adrenergic agonist drugs, can produce a significant cardiovascular effect in some patients, as measured by pulse rate, blood pressure, symptoms, and/or ECG changes.

Albuterol is longer acting than isoproterenol in most patients by any route of administration because it is not a substrate for the cellular uptake processes for catecholamines nor for catechol-O-methyl transferase.

The effects of rising doses of albuterol and isoproterenol areosols were studied in volunteers and asthmatic patients. Results in normal volunteers indicated that the propensity for increase in heart rate for albuterol is 1/2 to 1/4 that of isoproterenol. In asthmatic patients similar cardiovascular differentiation between the MO drugs was also seen.

Pharmacokinetics

Preclinical: Intravenous studies in rats with albuterol sulfate have demonstrated that albuterol crosses the blood-brain barrier and reaches brain concentrations that are amounting to approximately 5.0% of the plasma concentrations. In structures outside the brain barrier (pineal and pituitary glands), albuterol concentrations were found to be 100 times those in the whole brain.

Studies in laboratory animals (minipigs, rodents, and dogs) have demonstrated the occurrence of cardiac arrhythmias and sudden death (with histologic evidence of myocardial necrosis) when beta-agonists and methylxanthines were administered concurrently. The significance of these findings is unknown.

Pharmacokinetics

After either IPPB or nebulizer administration in asthmatic patients, less than 20% of a single albuterol dose was absorbed; the remaining amount was recovered from the nebulizer and apparatus and expired air. Most of the absorbed dose was recovered in the urine 24 hours after drug administration. Following a 3.0 mg dose of nebulized albuterol, the maximum albuterol plasma level at 0.5 hour was 2.1 ng/mL (range 1.4 to 3.2 ng/mL). It has been demonstrated that following oral administration of 4 mg of albuterol, the elimination half-life was 5 to 6 hours.

Clinical Trials:

In controlled clinical trials, most patients exhibited an onset of improvement in pulmonary function within 5 minutes as determined by FEV1. FEV1measurements also showed that the maximum average improvement in pulmonary function usually occurred at approximately 1 hour following inhalation of 2.5 mg of albuterol by compressor-nebulizer and remained close to peak for 2 hours. Clinically significant improvement in pulmonary function (defined as maintenance of a 15% or more increase in FEV1over baseline values) continued for 3 to 4 hours in most patients and in some patients continued up to 6 hours.

INDICATIONS AND USAGE

Albuterol sulfate inhalation solution is indicated for the relief of bronchospasm in patients 12 years of age and older with reversible obstructive airway disease and acute attacks of bronchospasm.

CONTRAINDICATIONS

Albuterol sulfate inhalation solution is contraindicated in patients with a history of hypersensitivity to albuterol or any of its components.

WARNINGS

DETERIORATION OF ASTHMA

Asthma may deteriorate acutely over a period of hours or chronically over several days or longer. If the patient needs more doses of albuterol sulfate inhalation solution than usual, this may be a marker of destabilization of asthma and requires re-evaluation of the patient and treatment regimen, giving special consideration to the possible need for anti-inflammatory treatment, e.g., corticosteroids.

USE OF ANTI-INFLAMMATORY AGENTS

The use of beta-adrenergic agonist bronchodilators alone may not be adequate to control asthma in many patients. Early consideration should be given to adding anti-inflammatory agents, e.g., corticosteroids.

PARADOXICAL BRONCHOSPASM

Albuterol sulfate inhalation solution can produce paradoxical bronchospasm, which may be life threatening. If paradoxical bronchospasm occurs, albuterol sulfate inhalation solution should be discontinued immediately and alternative therapy instituted. It should be recognized that paradoxical bronchospasm, when associated with inhaled formulations, frequently occurs with the first use of a new vial.

CARDIOVASCULAR EFFECTS

Albuterol sulfate inhalation solution, like all other beta-adrenergic agonists, can produce a clinically significant cardiovascular effect in some patients as measured by pulse rate, blood pressure, and/or symptoms. Although such effects are uncommon after administration of albuterol sulfate inhalation solution at recommended doses, if they occur, the drug may need to be discontinued. In addition, beta-agonists have been reported to produce electrocardiogram (ECG) changes, such as flattening of the T wave, prolongation of the QTc interval, and ST segment depression. The clinical significance of these findings is unknown. Therefore, albuterol sulfate inhalation solution, like all sympathomimetic amines, should be used with caution in patients with cardiovascular disorders, especially coronary insufficiency, cardiac arrhythmias, and hypertension.

IMMEDIATE HYPERSENSITIVITY REACTIONS

Immediate hypersensitivity reactions may occur after administration of albuterol, as demonstrated by rare cases of urticaria, angioedema, rash, bronchospasm, anaphylaxis, and oropharyngeal edema.

PRECAUTIONS

General

Albuterol, as with all sympathomimetic amines, should be used with caution in patients with cardiovascular disorders, especially coronary insufficiency, cardiac arrhythmias, and hypertension; in patients with convulsive disorders, hyperthyroidism, or diabetes mellitus; and in patients who are unusually responsive to sympathomimetic amines. Clinically significant changes in systolic and diastolic blood pressure have been seen in individual patients and could be expected to occur in some patients after use of any beta-adrenergic bronchodilator.

Large doses of intravenous albuterol have been reported to aggravate pre-existing diabetes mellitus and ketoacidosis. As with other beta-agonist medications, albuterol may produce significant hypokalemia in some patients, possibly through intracellular shunting, which has the potential to produce adverse cardiovascular effects. The decrease is usually transient, not requiring potassium supplementation.

Informations for Patients

The action of albuterol sulfate inhalation solution may last up to 6 hours or longer. Albuterol sulfate inhalation solution should not be used more frequently than recommended. Do not increase the dose or frequency of albuterol sulfate inhalation solution without consulting your physician. If you find that treatment with albuterol sulfate inhalation solution becomes less effective for symptomatic relief, your symptoms become worse, and/or you need to use the product more frequently than usual, you should seek medical attention immediately. While you are using albuterol sulfate inhalation solution, other inhaled drugs and asthma medications should be taken only as directed by your physician. Common adverse effects include palpitations, chest pain, rapid heart rate, tremor or nervousness. If you are pregnant or nursing, contact your physician about use of albuterol sulfate inhalation solution. Effective use of albuterol sulfate inhalation solution includes an understanding of the way it should be administered. See illustrated Instructions for Use.

Mixing Different Inhalation Solutions

Drug compatibility (physical and chemical), efficacy, and safety of Albuterol Sulfate Inhalation Solution when mixed with other drugs in a nebulizer have not been established.

Drug Interactions

Other short-acting sympathomimetic aerosol bronchodilators or epinephrine should not be used concomitantly with albuterol sulfate inhalation solution.

Beta-Blockers

Beta-adrenergic receptor blocking agents not only block the pulmonary effect of beta-agonists, such as albuterol sulfate inhalation solution, but may produce severe bronchospasm in asthmatic patients. Therefore, patients with asthma should not normally be treated with beta-blockers. However, under certain circumstances (e.g., as prophylaxis after myocardial infarction), there may be no acceptable alternatives to the use of beta-adrenergic blocking agents in patients with asthma. In this setting, cardioselective beta-blockers could be considered, although they should be administered with caution.

Diuretics

The ECG changes and/or hypokalemia that may result from the administration of non-potassium sparing diuretics (such as loop or thiazide diuretics) can be acutely worsened by beta-agonists, especially when the recommended dose of the beta-agonist is exceeded. Although the clinical significance of these effects is not known, caution is advised in the co-administration of beta-agonists with non-potassium sparing diuretics.

Digoxin

Mean decreases of 16% to 22% in serum digoxin levels were demonstrated after single dose intravenous and oral administration of albuterol, respectively, to normal volunteers who had received digoxin for 10 days. The clinical significance of these findings for patients with obstructive airway disease who are receiving albuterol and digoxin on a chronic basis is unclear. Nevertheless, it would be prudent to carefully evaluate the serum digoxin levels in patients who are currently receiving digoxin and albuterol.

Monoamine Oxidase Inhibitors or Tricyclic Antidepressants:

Albuterol sulfate inhalation solution should be administered with extreme caution to patients being treated with monoamine oxidase inhibitors or tricyclic antidepressants or within 2 weeks of discontinuation of such agents, because the action of albuterol on the vascular system may be potentiated.

Carcinogenesis, Mutagenesis, and Impairment of Fertility

In a 2-year study in Sprague-Dawley rats, albuterol sulfate caused a significant dose-related increase in the incidence of benign leiomyomas of the mesovarium at and above dietary doses of 2 mg/kg (approximately 2 times the maximum recommended daily inhalation dose for adults on a mg/m^2basis). In another study, this effect was blocked by the co-administration of propranolol, a non-selective beta-adrenergic antagonist.

In an 18-month study in CD-1 mice, albuterol sulfate showed no evidence of tumorigenicity at dietary doses up to 500 mg/kg (approximately 200 times the maximum recommended daily inhalation dose for adults on a mg/m^2basis). In a 22-month study in the Golden hamster, albuterol sulfate showed no evidence of tumorigenicity at dietary doses up to 50 mg/kg (approximately 25 times the maximum recommended daily inhalation dose for adults on a mg/m^2basis).

Albuterol sulfate was not mutagenic in the Ames test with or without metabolic activation using tester strains S. typhimuriumTA1537, TA1538, and TA98 or E. coliWP2, WP2uvrA, and WP67. No forward mutation was seen in yeast strain S. cerevisiaeS9 nor any mitotic gene conversion in yeast strain S. cerevisiaeJD1 with or without metabolic activation. Fluctuation assays in S. typhimuriumTA98 and E. coliWP2, both with metabolic activation, were negative. Albuterol sulfate was not clastogenic in a human peripheral lymphocyte assay or in an AH1 strain mouse micronucleus assay.

Reproduction studies in rats demonstrated no evidence of impaired fertility at oral doses of albuterol sulfate up to 50 mg/kg (approximately 40 times the maximum recommended daily inhalation dose for adults on a mg/m^2basis).

Pregnancy

Teratogenic Effects

Albuterol has been shown to be teratogenic in mice. A study in CD-1 mice at subcutaneous doses at and above 0.25 mg/kg (corresponding to less than the maximum recommended daily inhalation dose for adults on a mg/m^2basis), induced cleft palate formation in 5 of 111 (4.5%) fetuses. At an subcutaneous dose of 2.5 mg/kg (approximately equal to the maximum recommended daily inhalation dose for adults on mg/m^2basis), albuterol sulfate induced cleft palate formation in 10 of 108 (9.3%) fetuses. The drug did not induce cleft palate formation when administered at an subcutaneous dose of 0.025 mg/kg (corresponding to less than the maximum recommended daily inhalation dose for adults on mg/m^2basis). Cleft palate also occurred in 22 of 72 (30.5%) fetuses from females treated with 2.5 mg/kg isoproterenol (positive control) admnistered subcutaneously.

A reproduction study in Stride Dutch rabbits revealed cranioschisis in 7 of 19 (37%) fetuses when albuterol was administered orally at a dose of 50 mg/kg dose (approximately 80 times the maximum recommended daily inhalation dose for adults on a mg/m^2basis).

Studies in pregnant rats with titrated Albuterol demonstrated that approximately 10% of the circulating maternal drug is transferred to the fetus. Disposition in the fetal lungs is comparable to maternal lungs; but fetal liver disposition is 1% of the maternal liver levels.

There are no adequate and well-controlled studies in pregnant women. Because animal reproduction studies are not always predictive of human response. Albuterol should be used during pregnancy only if the potential benefit justifies the potential risk to the fetus.

During worldwide marketing experience, various congenital anomalies, including cleft palate and limb defects, have been reported in the offspring of patients being treated with albuterol. Some of the mothers were taking multiple medications during their pregnancies. No consistent pattern of defects can be discerned, and a relationship between albuterol use and congenital anomalies has not been established.

Labor and Delivery

Tocolysis:

Because of the potential for beta-agonist interference with uterine contractility, use of albuterol sulfate inhalation solution for relief of bronchospasm during labor should be restricted to those patients in whom the benefits clearly outweigh the risk.

Albuterol has not been approved for the management of preterm labor. The benefit:risk ratio when albuterol is administered for tocolysis has not been established. Serious adverse reactions, including maternal pulmonary edema, have been reported during or following treatment of premature labor with beta2-agonists, including albuterol.

Nursing Mothers

It is not known whether this drug is excreted in human milk. Because of the potential for tumorigenicity shown for albuterol in some animal studies, a decision should be made whether to discontinue nursing or to discontinue the drug, taking into account the importance of the drug to the mother.

Pediatric Use

Safety and effectiveness of albuterol inhalation solution and solution for inhalation in children below the age of 12 years have not been established.

ADVERSE REACTIONS

The results of clinical trials with albuterol sulfate inhalation solution in 135 patients showed the following side effects which were considered probably or possibly drug related:

Percent Incidence of Adverse Reactions
Reaction | Percent Incidence; (N=135)
Central Nervous System
Tremors | 20
Dizziness | 7
Nervousness | 4
Headache | 3
Insomnia | 1
Gastrointestinal
Nausea | 4
Dyspepsia | 1
Ear, nose and throat; Nasal congestion | 1
Pharyngitis | <1
Cardiovascular
Tachycardia | 1
Hypertensions | 1
Respiratory
Bronchospasm | 8
Cough | 4
Bronchitis | 4
Wheezing | 1

No clinically relevant laboratory abnormalities related to albuterol sulfate inhalation solution were determined in these studies.

Cases of urticaria, angioedema, rash, bronchospasm, hoarseness, oropharyngeal edema, and arrhythmias (including atrial fibrillation, supraventricular tachycardia, and extrasystoles) have also been reported after the use of inhaled albuterol.

To report SUSPECTED ADVERSE REACTIONS, contact Ritedose Pharmaceuticals, LLC at 1-855-806-3300 or FDA at 1-800-FDA-1088 or www.fda.gov/medwatch.

OVERDOSAGE

The expected symptoms with overdosage are those of excessive beta-adrenergic stimulation and/or occurrence or exaggeration of any of the symptoms listed under ADVERSE REACTIONS, e.g., angina, hypertension, tachycardia with rates up to 200 beats per minute, arrhythmias, nervousness, headache, tremor, dry mouth, palpitation, nausea, dizziness, malaise, and insomnia. In addition, seizures, hypotension, fatigue, and hypokalemia may also occur. As with all sympathomimetic aerosol medications, cardiac arrest and even death may be associated with abuse of albuterol sulfate inhalation solution. Treatment consists of discontinuation of albuterol sulfate inhalation solution together with appropriate symptomatic therapy. The judicious use of a cardioselective beta-receptor blocker may be considered bearing in mind that such medication can produce bronchospasm. There is insufficient evidence to determine if dialysis is beneficial for overdosage of albuterol sulfate inhalation solution.

The oral median lethal dose of albuterol sulfate in mice is greater than 2000 mg/kg (approximately 810 times the maximum recommended daily inhalation dose for adults on a mg/m^2basis). In mature rats, the subcutaneous median lethal dose of albuterol sulfate is approximately 450 mg/kg (approximately 360 times the maximum recommended daily inhalation dose for adults on a mg/m^2basis). In small young rats, the subcutaneous median lethal dose of albuterol sulfate is approximately 2000 mg/kg (approximately 1600 times the maximum recommended daily inhalation dose for adults on a mg/m^2basis). The inhalation median lethal dose has not been determined in animals.

DOSAGE AND ADMINISTRATION

The usual dosage for adults and pediatric patients 12 years of age and older is 2.5 mg of albuterol (one unit-of-use vial) administered 3 to 4 times daily by nebulization. More frequent administration or higher doses are not recommended. To administer 2.5 mg of albuterol, dilute 0.5 mL of the 0.5% solution for inhalation to a total volume of 3 mL with sterile normal saline solution and administer by nebulization. The flow rate is regulated to suit the particular nebulizer so that albuterol sulfate inhalation solution will be delivered over approximately 5 to 15 minutes.

Drug compatibility (physical and chemical), efficacy, and safety of albuterol sulfate inhalation solution when mixed with other drugs in a nebulizer have not been established.

The use of albuterol sulfate inhalation solution can be continued as medically indicated to control recurring bouts of bronchospasm. During treatment, most patients gain optimum benefit from regular use of the nebulizer solution.

If a previously effective dosage regimen fails to provide the usual relief, medical advice should be sought immediately, as this is often a sign of seriously worsening asthma which would require reassessment of therapy.

The nebulizer should be cleaned in accordance with the manufacturer’s instructions. Failure to do so could lead to bacterial contamination of the nebulizer and possible infection.

HOW SUPPLIED

Albuterol Sulfate Inhalation Solution, 2.5 mg/0.5 mL (equivalent to 3 mg albuterol sulfate), is a clear, colorless to light yellow solution, and is supplied in plastic sterile unit-dose vials of 0.5 mL each, supplied in individual foil pouches:

NDC 76204-027-01: 30 unit-dose vials, each in an individual pouch.

Storage and Handling

Store between 2°C and 25°C (36°F – 77°F). Protect from light. Store in a pouch until time of use.

Rx Only

Manufactured for:

Ritedose Pharmaceuticals, LLC

Columbia, SC 29203

Manufactured by:

The Ritedose Corporation

Columbia, SC 29203

March 2024

INSTRUCTIONS FOR USE

Albuterol Sulfate Inhalation Solution

2.5 mg/0.5 mL (equivalent to 3 mg albuterol sulfate)

Note: The Albuterol Sulfate Inhalation Solution is concentrated and must be diluted.

Read complete instructions carefully before using.

1. Twist open the top of one Albuterol Sulfate Inhalation Solution unit-of-use container (Figure 1).

FIGURE 1

2. Squeeze the solution into the nebulizer reservoir through the appropriate opening (Figure 2).

FIGURE 2

3. Add 2.5 mL of diluting fluid – sterile normal saline solution (as your doctor has directed).4. Gently swirl the nebulizer to mix the contents and connect it with the mouthpiece or face mask (Figure 3).

FIGURE 3

5. Connect the nebulizer to the compressor.

6. Sit in a comfortable, upright position; place the mouthpiece in your mouth (Figure 4) (or put on the face mask); and turn the compressor on.

FIGURE 4

7. Breathe as calmly, deeply, and evenly as possible until no more mist is formed in the nebulizer chamber (about 5 to 15 minutes). At this point, the treatment is finished.

8. Clean the nebulizer (see manufacturer’s instructions). Failure to clean the nebulizer in accordance with the manufacturer’s instructions could lead to bacterial contamination of the nebulizer, and possible infection.

Note: Use only as directed by your physician. More frequent administration or higher doses are not recommended.

Mixing Compatibility: The safety and effectiveness of Albuterol sulfate solution for inhalation have not been determined when one or more drugs are mixed with it in a nebulizer.

Store Albuterol Sulfate Inhalation Solution, 0.5%, between 2° and 25° C (36° and 77° F).

ADDITIONAL INSTRUCTIONS________________________________

______________________________________________________

______________________________________________________

______________________________________________________

______________________________________________________

This Instructions for Use has been approved by the U.S. Food and Drug Administration.

Manufactured for:

Ritedose Pharmaceuticals, LLC

Columbia, SC 29203

Manufactured by:

The Ritedose Corporation

Columbia, SC 29203

March 2024